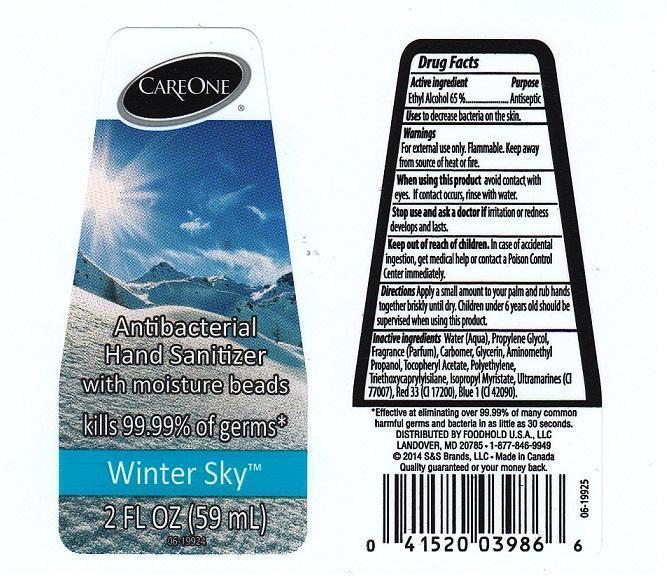 DRUG LABEL: CAREONE
NDC: 41520-503 | Form: LIQUID
Manufacturer: AMERICAN SALES COMPANY
Category: otc | Type: HUMAN OTC DRUG LABEL
Date: 20140815

ACTIVE INGREDIENTS: ALCOHOL 650 mg/1 mL
INACTIVE INGREDIENTS: WATER; PROPYLENE GLYCOL; CARBOMER 934; GLYCERIN; AMINOMETHYLPROPANOL; .ALPHA.-TOCOPHEROL ACETATE; HIGH DENSITY POLYETHYLENE; TRIETHOXYCAPRYLYLSILANE; ISOPROPYL MYRISTATE; ULTRAMARINE BLUE; D&C RED NO. 33; FD&C BLUE NO. 1

DRUG FACTS

ACTIVE INGREDIENT

ETHYL ALCOHOL 65%

PURPOSE

ANTISEPTIC

USES

TO DECREASE BACTERIA ON THE SKIN

WARNINGS

FOR EXTERNAL USE ONLY. FLAMMABLE. KEEP AWAY FROM SOURCE OF HEAT OR FIRE

WHEN USING THIS PRODUCT

AVOID CONTACT WITH EYES. IF CONTACT OCCURS, RINSE WITH WATER

STOP USE AND ASK A DOCTOR IF

IRRITATION OR REDNESS DEVELOPS AND LASTS

KEEP OUT OF REACH OF CHILDREN

IN CASE OF ACCIDENTAL INGESTION, GET MEDICAL HELP OR CONTACT A POISON CONTROL CENTER IMMEDIATELY

DIRECTIONS

APPLY A SMALL AMOUNT TO YOUR PALM AND RUB HANDS TOGETHER BRISKLY UNTIL DRY. CHILDREN UNDER 6 YEARS OLD SHOULD BE SUPERVISED WHEN USING THIS PRODUCT

INACTIVE INGREDIENTS

WATER (AQUA), PROPYLENE GLYCOL, FRAGRANCE (PARFUM), CARBOMER, GLYCERIN, AMINOMETHYL PROPANOL, TOCOPHERYL ACETATE, POLYETHYLENE, TRIETHOXYCAPRYLYLSILANE, ISOPROPYL MYRISTATE, ULTRAMARINES (CI 77007), RED 33 (CI 17200), BLUE 1 (CI 42090)